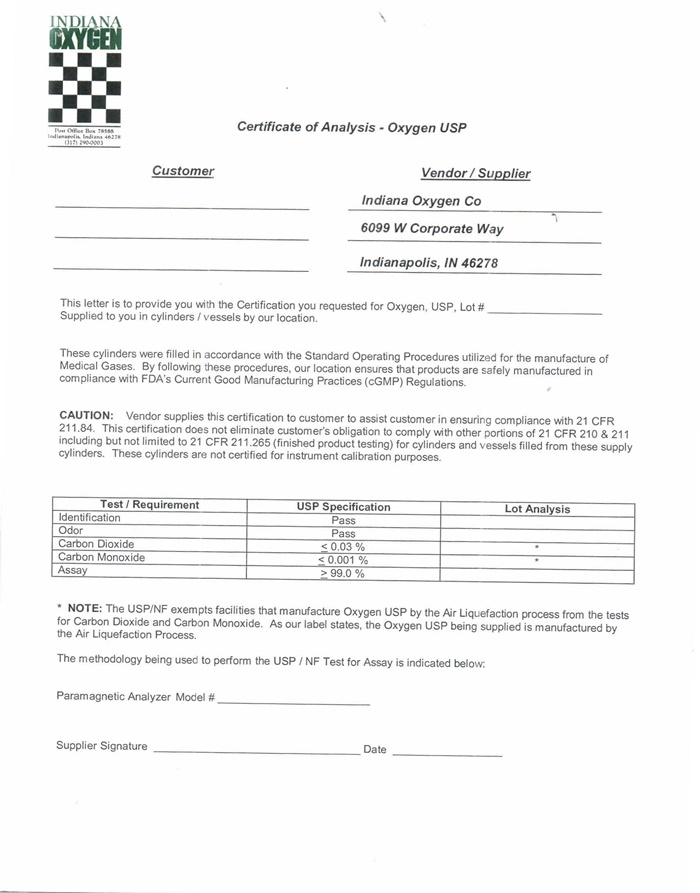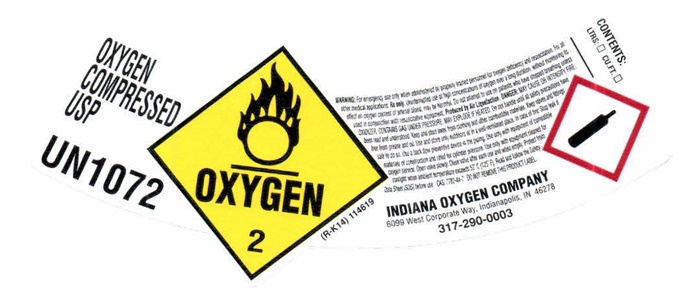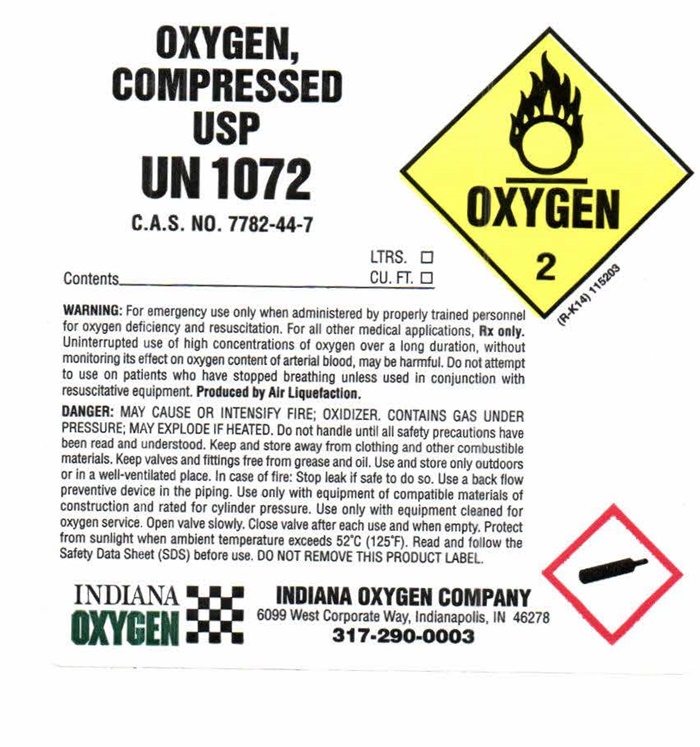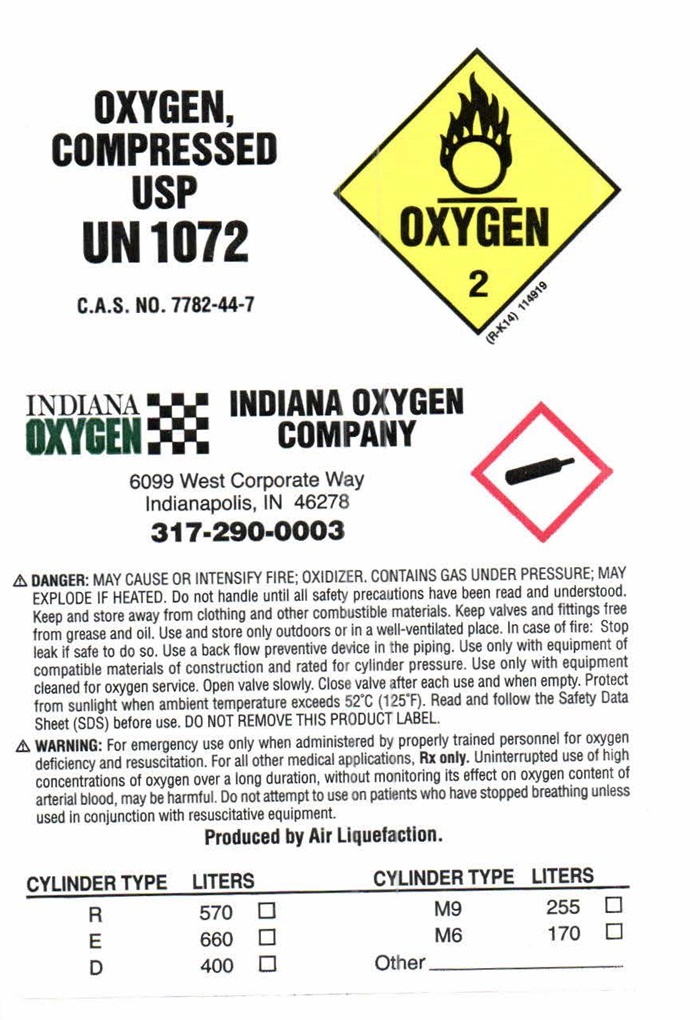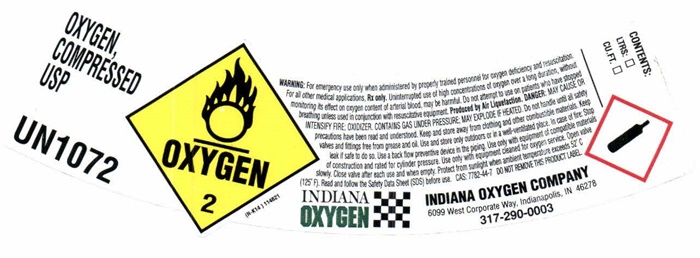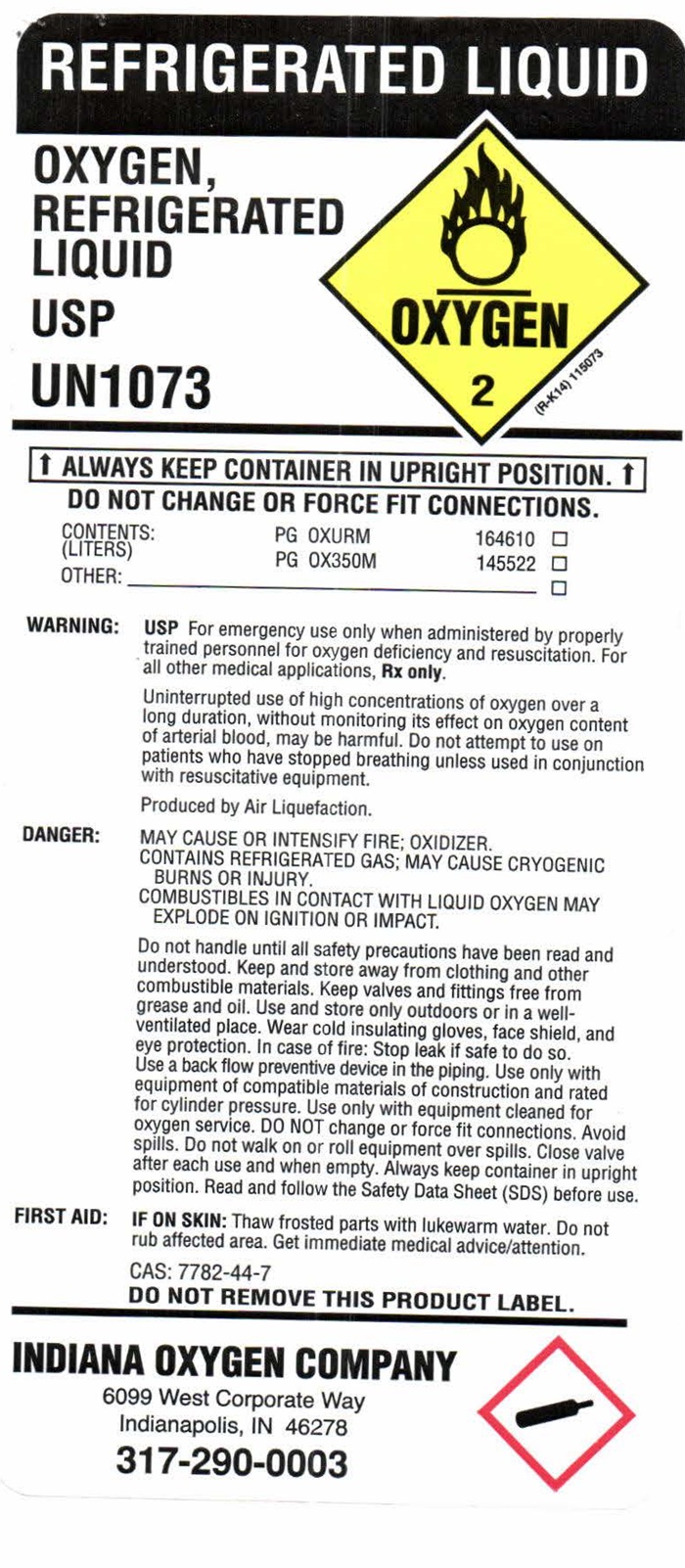 DRUG LABEL: OXYGEN
NDC: 48546-0001 | Form: GAS
Manufacturer: Indiana Oxygen Company Inc
Category: prescription | Type: HUMAN PRESCRIPTION DRUG LABEL
Date: 20241023

ACTIVE INGREDIENTS: OXYGEN 99 L/100 L

Oxygen

OXYGEN COMPRESSED LABEL

OXYGEN COMPRESSED USP
UN 1072
OXYGEN 2
(R-K14) 114619

WARNING: For emergency use only when administered by properly trained personnel for oxygen deficiency and resuscitation. For all other medical applications, Rx only. Uninterrupted use of high concentrations of oxygen over a long duration, without monitoring its effect on oxygen content of arterial blood, may be harmful. Do not attempt to use on patients who have stopped breathing unless in conjunction with resuscitative equipment. Produced by Air Liquefaction.

DANGER: MAY CAUSE OR INTENSIFY FIRE; OXIDIZER, CONTAINS GAS UNDER PRESSURE; MAY EXPLODE IF HEATED. Do not handle until all safety precautions have been read and understood. Keep and store away from clothing and other combustible materials. Keep valves and fittings free from grease and oil. Use and store only outdoors or in a well-ventilated place. In case of fire: Stop leak if safe to do so. Use a back flow preventive device in the pping. Use only with equipment of compatible materials of construction and rated for cylinder pressure. Use only with equipment cleaned for oxygen service. Open valve slowly. Close valve after each use and when empty. Protect from sunlight and when the ambient temperature exceeds 52°C (125°F). Read and follow the Safety Data Sheet (SDS) before use. CAS: 7782-44-7 DO NOT REMOVE THIS PRODUCT LABEL.

INDIANA OXYGEN COMPANY
6099 West Corporate Way, Indianapolis, IN 462278
317-290-0003

CONTENTS:
LTRS: _____ CU. FT. _____

OXYGEN COMPRESSED USP
UN 1072
OXYGEN 2
(R-K14) 114621

WARNING: For emergency use only when administered by properly trained personnel for oxygen deficiency and resuscitation. For all other medical applications, Rx only. Uninterrupted use of high concentrations of oxygen over a long duration, without monitoring its effect on oxygen content of arterial blood, may be harmful. Do not attempt to use on patients who have stopped breathing unless in conjunction with resuscitative equipment. Produced by Air Liquefaction.

DANGER: MAY CAUSE OR INTENSIFY FIRE; OXIDIZER, CONTAINS GAS UNDER PRESSURE; MAY EXPLODE IF HEATED. Do not handle until all safety precautions have been read and understood. Keep and store away from clothing and other combustible materials. Keep valves and fittings free from grease and oil. Use and store only outdoors or in a well-ventilated place. In case of fire: Stop leak if safe to do so. Use a back flow preventive device in the pping. Use only with equipment of compatible materials of construction and rated for cylinder pressure. Use only with equipment cleaned for oxygen service. Open valve slowly. Close valve after each use and when empty. Protect from sunlight and when the ambient temperature exceeds 52°C (125°F). Read and follow the Safety Data Sheet (SDS) before use. CAS: 7782-44-7 DO NOT REMOVE THIS PRODUCT LABEL.

INDIANA OXYGEN COMPANY
6099 West Corporate Way, Indianapolis, IN 462278
317-290-0003

CONTENTS:
LTRS: _____ CU. FT. _____

OXYGEN COMPRESSED USP
UN 1072
C.A.S. NO. 7782-44-7

Contents ______________________ LTRS. __________ CU. FT. __________

OXYGEN 2
(R-K14) 11623

WARNING: For emergency use only when administered by properly trained personnel for oxygen deficiency and resuscitation. For all other medical applications, Rx only. Uninterrupted use of high concentrations of oxygen over a long duration, without monitoring its effect on oxygen content of arterial blood, may be harmful. Do not attempt to use on patients who have stopped breathing unless in conjunction with resuscitative equipment. Produced by Air Liquefaction.

DANGER: MAY CAUSE OR INTENSIFY FIRE; OXIDIZER, CONTAINS GAS UNDER PRESSURE; MAY EXPLODE IF HEATED. Do not handle until all safety precautions have been read and understood. Keep and store away from clothing and other combustible materials. Keep valves and fittings free from grease and oil. Use and store only outdoors or in a well-ventilated place. In case of fire: Stop leak if safe to do so. Use a back flow preventive device in the pping. Use only with equipment of compatible materials of construction and rated for cylinder pressure. Use only with equipment cleaned for oxygen service. Open valve slowly. Close valve after each use and when empty. Protect from sunlight and when the ambient temperature exceeds 52°C (125°F). Read and follow the Safety Data Sheet (SDS) before use. DO NOT REMOVE THIS PRODUCT LABEL.

INDIANA OXYGEN COMPANY
6099 West Corporate Way, Indianapolis, IN 462278
317-290-0003

OXYGEN COMPRESSED USP
UN 1072
C.A.S. NO. 7782-44-7

OXYGEN 2
(R-K14) 114919

INDIANA OXYGEN COMPANY
6099 West Corporate Way, Indianapolis, IN 462278
317-290-0003

DANGER: MAY CAUSE OR INTENSIFY FIRE; OXIDIZER, CONTAINS GAS UNDER PRESSURE; MAY EXPLODE IF HEATED. Do not handle until all safety precautions have been read and understood. Keep and store away from clothing and other combustible materials. Keep valves and fittings free from grease and oil. Use and store only outdoors or in a well-ventilated place. In case of fire: Stop leak if safe to do so. Use a back flow preventive device in the pping. Use only with equipment of compatible materials of construction and rated for cylinder pressure. Use only with equipment cleaned for oxygen service. Open valve slowly. Close valve after each use and when empty. Protect from sunlight and when the ambient temperature exceeds 52°C (125°F). Read and follow the Safety Data Sheet (SDS) before use. DO NOT REMOVE THIS PRODUCT LABEL.

WARNING: For emergency use only when administered by properly trained personnel for oxygen deficiency and resuscitation. For all other medical applications, Rx only. Uninterrupted use of high concentrations of oxygen over a long duration, without monitoring its effect on oxygen content of arterial blood, may be harmful. Do not attempt to use on patients who have stopped breathing unless in conjunction with resuscitative equipment.

Produced by Air Liquefaction.

CYLINDER TYPE LITERS CYLINDER TYPE LITERS
R 570 M9 255
E 660 M6 170
D 400 Other ____________

OXYGEN REFRIGERATED LABEL

REFRIGERATED LIQUID

OXYGEN,
REFRIGERATED
LIQUID
USP

UN 1073

OXYGEN 2
(R-K14) 115073

↑ALWAYS KEEP CONTAINER IN UPRIGHT POSITION.↑
DO NOT CHANGE OR FORCE FIT CONNECTIONS.

CONTENTS: PG OXURM 164610
(LITERS) PG OX35OM 145522

WARNING: USP For emergency use only when administered by properly trained personnel for oxygen deficiency and resuscitation. For all other medical applications, Rx only.

Uninterrupted use of high concentrations of oxygen over a long duration, without monitoring its effect on oxygen content of arterial blood, may be harmful. Do not attempt to use on patients who have stopped breathing unless in conjunction with resuscitative equipment.

Produced by Air Liquefaction.

DANGER: MAY CAUSE OR INTENFIFY FIRE: OXIDIZER.
CONTAINS REFRIGERATED GAS; MAY CAUSE CRYOGENIC BURNS OR INJURY
COMBUSTIBLES IN CONTACT WITH LIQUIDE OXYGEN MAY EXPLODE ON IGNITION OT IMPACT.

Do not handle until all safety precautions have been read and understood. Keep and store away from clothing and other combustible materials. Keep valves and fittings free from grease and oil. Use and store only outdoors or in a well-ventilated place. Wear cold insulating gloves, face shield and eye protection. In case of fire: Stop leak if safe to do so. Use a back flow preventive device in the pping. Use only with equipment of compatible materials of construction and rated for cylinder pressure. Use only with equipment cleaned for oxygen service. DO NOY change of force fit connections. Avoid spills. Do not walk or roll equipment over spills. Close valve after wach use and when empty. Always keep container in upright position. Read and follow the Safety Data Sheet (SDS) before use.

FIRST AID: IF ON SKIN: Thaw frosted parts with lukewarm water. Do not rub affected area. Get immediate medical advise/attention.

CAS: 7782-44-7
DO NOT REMOVE THIS PRODUCT LABEL.

INDIANA OXYGEN COMPANY
6099 West Corporate Way, Indianapolis, IN 462278
317-290-0003

OXYGEN CERTIFICATE OF ANALYSIS

Certificate of Analysis - Oxygen USP

CUSTOMER ___________________ VENDOR / SUPPLIER ________________________

____________________________ Indiana Oxygen Co
____________________________ 6099 W Corporate Way
____________________________ Indianapolis, IN 46278

THIS LETTER IS TO PROVIDE YOU WITH THE CERTIFICATION YOU REQUESTED FOR OXYGEN USP LOT # _______________________
SUPPLIED TO YOU IN CYLINDERS / VESSELS BY OUR LOCATION.

These cylinders were filled in accordance with the Standard Operating Procedures utilized for the manufacture of Medical Gases. By following these procedures, our location ensures that products are safely manufactured in compliance with FDA’s Current Good Manufacturing Practices (cGMP) Regulations.

CAUTION: VENDOR SUPPLIES THIS CERTIFICATION TO CUSTOMER TO ASSIST CUSTOMER INENSURING COMPLIANCE WITH 21 CFR 211.84. THIS CERTIFICATION DOES NOT ELIMINATE CUSTOMERS OBLIGATION TO COMPLY WITHOTHER PORTIONS OF 21 CFR 210 AND 211, INCLUDING BUT NOT LIMITED TO 21 CFR 211.165 (FINISHED PRODUCT TESTING) FOR CYLINDERS AND VESSELS FILLED FROM THESE SUPPLY CYLINDERS. THESE CYLINDERS ARE NOT CERTIFIED FOR INSTRUMENT CALIBRATION.

TEST REQUIREMENT USP SPECIFICATION LOT ANALYSIS
IDENTIFICATION PASS
ODOR PASS
CARBON DIOXIDE LESS THAT 0.03%
CARBON MONOXIDE LESS THAT 0.001%
ASSAY GREATER THAN 99.0%

* NOTE: The USP/NF exempts facilities that manufacture Oxygen USP by the Air Liquefaction process from the tests for Carbon Dioxide and Carbon Monoxide. As our label states, the Oxygen USP being supplied is manufactured by the Air Liquefaction Process.

The methodology being used to perform the USP / NF Test for Assay is indicated below:

Paramagnetic Analyzer Model # _________________________

Supplier Signature ___________________________ Date _____________